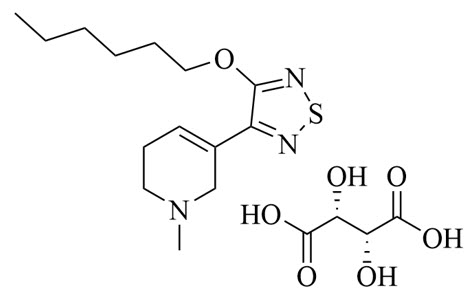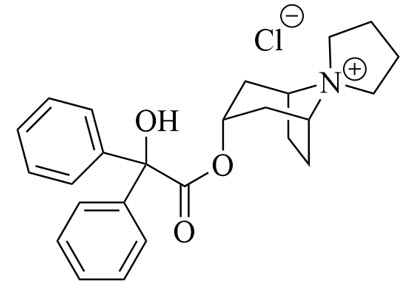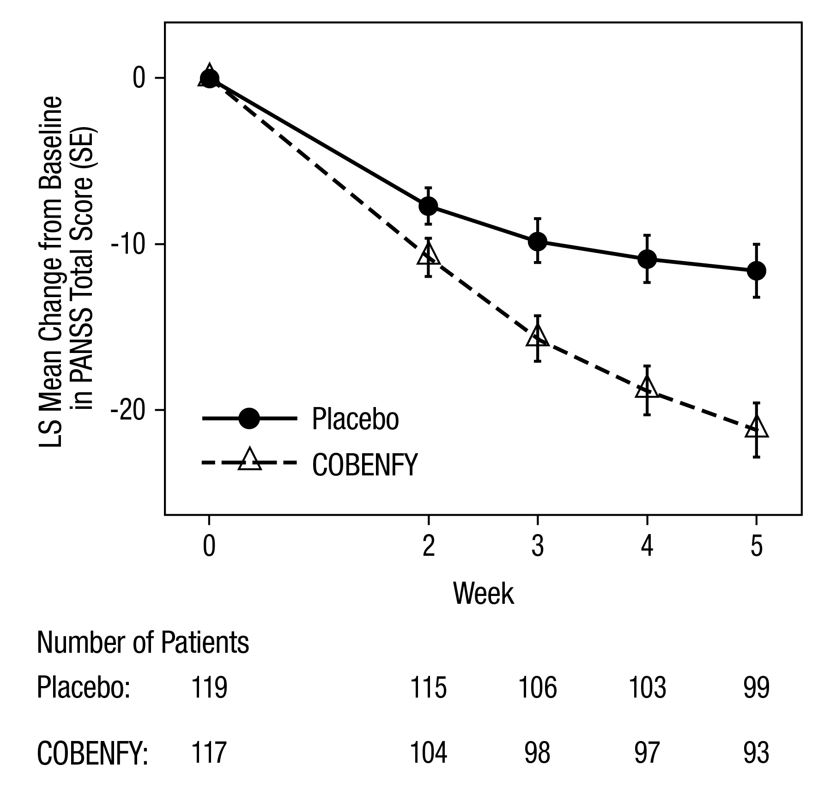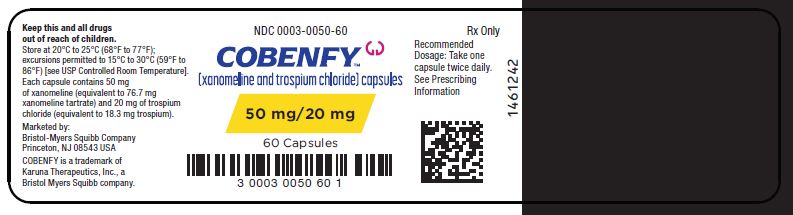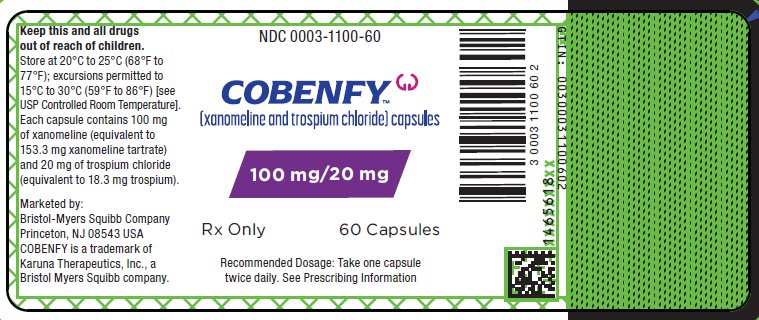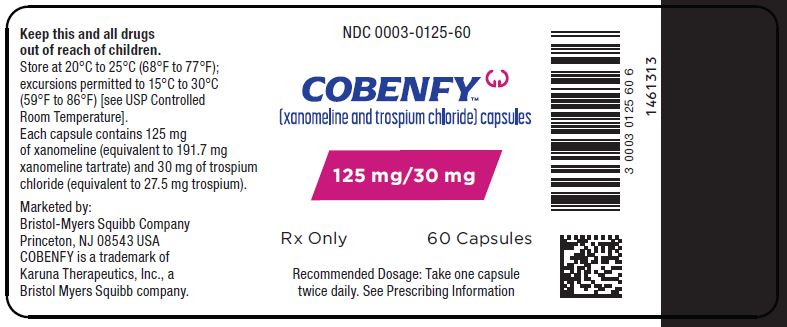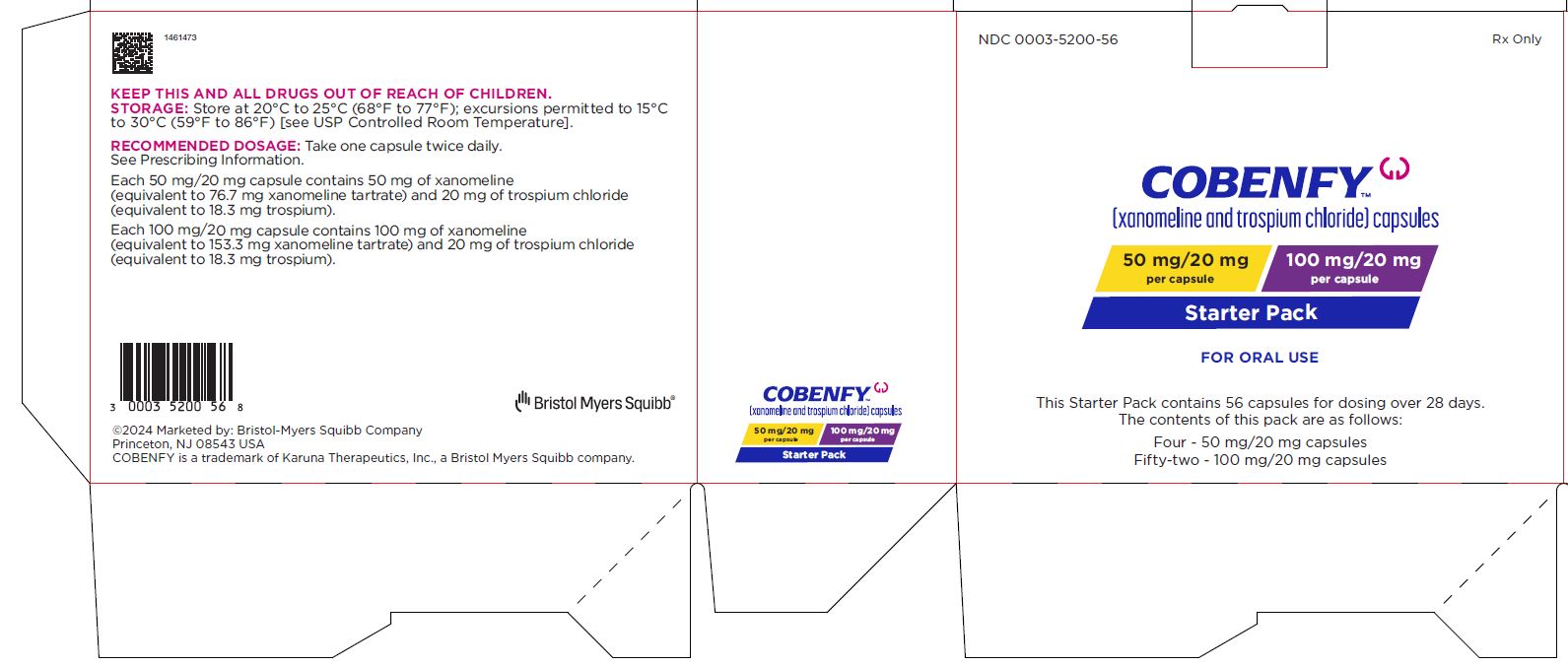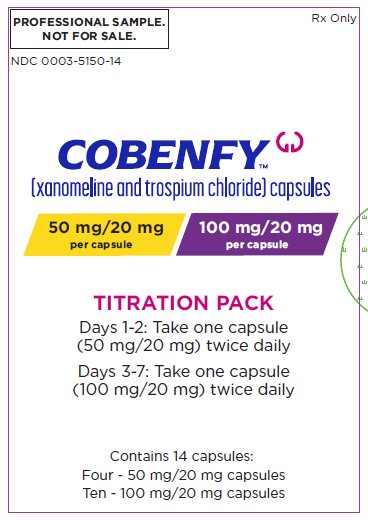 DRUG LABEL: Cobenfy
NDC: 0003-0050 | Form: CAPSULE, COATED PELLETS
Manufacturer: E.R. Squibb & Sons, L.L.C.
Category: prescription | Type: HUMAN PRESCRIPTION DRUG LABEL
Date: 20260116

ACTIVE INGREDIENTS: xanomeline 50 mg/1 1; trospium chloride 20 mg/1 1
INACTIVE INGREDIENTS: microcrystalline cellulose; ascorbic acid; talc; lactose monohydrate; hypromellose, unspecified; titanium dioxide; ferric oxide red; ferric oxide yellow

HIGHLIGHTS OF PRESCRIBING INFORMATION

These highlights do not include all the information needed to use COBENFY safely and effectively. See full prescribing information for COBENFY.
COBENFY™ (xanomeline and trospium chloride) capsules, for oral use
Initial U.S. Approval: 2024

1 INDICATIONS AND USAGE

COBENFY is a combination of xanomeline, a muscarinic agonist, and trospium chloride, a muscarinic antagonist, indicated for the treatment of schizophrenia in adults. (1)

2 DOSAGE AND ADMINISTRATION

- Assess liver enzymes and bilirubin prior to initiating treatment with COBENFY and as clinically indicated during treatment. (2.1)
- Assess heart rate at baseline and as clinically indicated during treatment with COBENFY. (2.1)
- Recommended starting dosage of COBENFY is 50 mg/20 mg orally twice daily for at least two days, then increase the dosage to 100 mg/20 mg twice daily for at least five days. (2.2)
- Dosage may be increased to 125 mg/30 mg orally twice daily based on patient tolerability and response. (2.2)
- See the full prescribing information for the recommended titration and maximum recommended dosage. (2.2)
- Take at least 1 hour before a meal or at least 2 hours after a meal. Do not open capsules. (2.2)
- Geriatric patients: Recommended starting dosage of COBENFY is 50 mg/20 mg orally twice daily. Consider a slower titration. The maximum recommended dosage is 100 mg/20 mg twice daily. (2.3)

3 DOSAGE FORMS AND STRENGTHS

Capsules (xanomeline/trospium chloride): 50 mg/20 mg, 100 mg/20 mg, 125 mg/30 mg (3)

4 CONTRAINDICATIONS

COBENFY is contraindicated in:

- urinary retention (4)
- moderate or severe hepatic impairment (4)
- gastric retention (4)
- history of hypersensitivity to COBENFY or trospium chloride (4)
- untreated narrow-angle glaucoma (4)

5 WARNINGS AND PRECAUTIONS

- Risk of Urinary Retention: COBENFY can cause urinary retention. Geriatric patients and patients with bladder outlet obstruction and incomplete bladder emptying are at increased risk. Monitor patients for symptoms of acute urinary retention. (5.1)
- Risk of Use in Patients with Hepatic Impairment: COBENFY is contraindicated in patients with moderate to severe hepatic impairment and is not recommended in patients with mild hepatic impairment. (5.2)
- Risk of Use in Patients with Biliary Disease: Assess liver enzymes and bilirubin prior to initiating COBENFY and as clinically indicated. Discontinue COBENFY in the presence of signs or symptoms of substantial liver injury. (5.3)
- Decreased Gastrointestinal Motility: COBENFY may decrease gastrointestinal motility. Use with caution in patients with gastrointestinal obstructive disorders because of the risk of gastric retention. (5.4)
- Risk of Angioedema: Angioedema of the face, lips, tongue and/or larynx has been reported with COBENFY. (5.5)
- Risk of Use in Patients with Narrow-angle Glaucoma: Use COBENFY only if the potential benefits outweigh the risks and with careful monitoring. (5.6)
- Increases in Heart Rate: COBENFY may increase heart rate. Assess heart rate at baseline and as clinically indicated during treatment with COBENFY. (5.7)
- Anticholinergic Adverse Reactions in Patients with Renal Impairment: COBENFY is not recommended for use in patients with moderate and severe renal impairment. Anticholinergic adverse reactions are expected to be greater in these patients. (5.8)
- Central Nervous System Effects: COBENFY may be associated with CNS effects. Advise patients not drive or operate heavy machinery until they know how COBENFY affects them. (5.9)

6 ADVERSE REACTIONS

Most common adverse reactions (incidence ≥ 5% and at least twice placebo) were nausea, dyspepsia, constipation, vomiting, hypertension, abdominal pain, diarrhea, tachycardia, dizziness, and gastrointestinal reflux disease. (6.1)

To report SUSPECTED ADVERSE REACTIONS, contact Bristol-Myers Squibb at 1-800-721-5072 or FDA at 1-800-FDA-1088 or www.fda.gov/medwatch.

7 DRUG INTERACTIONS

- Drugs Eliminated by Active Tubular Secretion: Monitor for increased frequency and/or severity of adverse reactions related to COBENFY and to drugs eliminated by active tubular secretion. (7.1)
- Strong CYP2D6 Inhibitors: Monitor for increased frequency and/or severity of COBENFY-related adverse reactions. (7.1)
- Sensitive Substrates of CYP3A4 or P-glycoprotein: Monitor for increased frequency and/or severity of adverse reactions from these substrates. (7.1)
- Antimuscarinic Drugs: Monitor for increased frequency or severity of anticholinergic adverse reactions. (7.2)

8 USE IN SPECIFIC POPULATIONS

- Moderate or Severe Renal Impairment: Not recommended. (8.6)
- Mild Hepatic Impairment: Not recommended. (8.7)

FULL PRESCRIBING INFORMATION

1 INDICATIONS AND USAGE

COBENFY is indicated for the treatment of schizophrenia in adults.

2 DOSAGE AND ADMINISTRATION

2.1 Recommended Testing and Monitoring Prior to Initiation and During Treatment with COBENFY

- Assess liver enzymes and bilirubin prior to initiating COBENFY and as clinically indicated during treatment [see Contraindications (4) and Warnings and Precautions (5.2, 5.3)].
- Assess heart rate at baseline and as clinically indicated during treatment [see Warnings and Precautions (5.7)].

2.2 Recommended Dosage and Administration

The recommended dosage of COBENFY is as follows:

- The recommended starting dosage is one 50 mg/20 mg capsule (contains 50 mg of xanomeline and 20 mg of trospium chloride) orally twice daily for at least two days.
- Increase the dosage to one 100 mg/20 mg capsule (contains 100 mg of xanomeline and 20 mg of trospium chloride) orally twice daily for at least five days.
- The dosage may be increased to one 125 mg/30 mg capsule (contains 125 mg of xanomeline and 30 mg of trospium chloride) orally twice daily based on patient tolerability and response [see Clinical Studies (14)].
- Maximum recommended dosage is 125 mg/30 mg orally twice daily.

Administer COBENFY orally at least one hour before a meal or at least two hours after a meal [see Clinical Pharmacology (12.3)]. Do not open the capsules.

2.3 Dosage Recommendations in Geriatric Patients

The recommended starting dosage of COBENFY in geriatric patients is one 50 mg/20 mg capsule orally twice daily. Consider a slower titration for geriatric patients. The maximum recommended dosage in geriatric patients is one 100 mg/20 mg capsule twice daily [see Warnings and Precautions (5.1, 5.8) and Use in Specific Populations (8.5)].

3 DOSAGE FORMS AND STRENGTHS

COBENFY is available as:

- 50 mg/20 mg (xanomeline/trospium chloride): Buff capsules imprinted with Karuna 50/20 mg
- 100 mg/20 mg (xanomeline/trospium chloride): Brown capsules imprinted with Karuna 100/20 mg
- 125 mg/30 mg (xanomeline/trospium chloride): Swedish Orange capsules imprinted with Karuna 125/30 mg

4 CONTRAINDICATIONS

COBENFY is contraindicated in patients with:

- urinary retention [see Warnings and Precautions (5.1)].
- moderate (Child-Pugh Class B) or severe (Child-Pugh Class C) hepatic impairment [see Warnings and Precautions (5.2)].
- gastric retention [see Warnings and Precautions (5.4)].
- history of hypersensitivity to COBENFY or trospium chloride. Angioedema has been reported with COBENFY and trospium chloride [see Warnings and Precautions (5.5)].
- untreated narrow-angle glaucoma [see Warnings and Precautions (5.6)].

5 WARNINGS AND PRECAUTIONS

5.1 Risk of Urinary Retention

COBENFY can cause urinary retention [see Adverse Reactions (6.1)]. Geriatric patients and patients with clinically significant bladder outlet obstruction and incomplete bladder emptying (e.g., patients with benign prostatic hyperplasia (BPH), diabetic cystopathy) may be at increased risk of urinary retention [see Use in Specific Populations (8.5)].

COBENFY is contraindicated in patients with pre-existing urinary retention [see Contraindications (4)] and is not recommended in patients with moderate or severe renal impairment [see Use in Specific Populations (8.6) and Clinical Pharmacology (12.3)].

In patients taking COBENFY, monitor for symptoms of urinary retention, including urinary hesitancy, weak stream, incomplete bladder emptying, and dysuria. Instruct patients to be aware of the risk and promptly report symptoms of urinary retention to their healthcare provider. Urinary retention is a known risk factor for urinary tract infections. In patients with symptoms of urinary retention, consider reducing the dose of COBENFY, discontinuing COBENFY, or referring patients for urologic evaluation as clinically indicated.

5.2 Risk of Use in Patients with Hepatic Impairment

Patients with hepatic impairment have higher systemic exposures of xanomeline, a component of COBENFY, compared to patients with normal hepatic function, which may result in increased incidence of COBENFY-related adverse reactions [see Clinical Pharmacology (12.3)].

COBENFY is contraindicated in patients with moderate or severe hepatic impairment [see Contraindications (4)]. COBENFY is not recommended in patients with mild hepatic impairment [see Use in Specific Populations (8.7) and Clinical Pharmacology (12.3)].

Assess liver enzymes prior to initiating COBENFY and as clinically indicated during treatment.

5.3 Risk of Use in Patients with Biliary Disease

In clinical studies with COBENFY, transient increases in liver enzymes with rapid decline occurred, consistent with transient biliary obstruction due to biliary contraction and possible gallstone passage [see Adverse Reactions (6.1)].

COBENFY is not recommended for patients with active biliary disease such as symptomatic gallstones. Assess liver enzymes and bilirubin prior to initiating COBENFY and as clinically indicated during treatment. The occurrence of symptoms such as dyspepsia, nausea, vomiting, or upper abdominal pain should prompt assessment for gallbladder disorders, biliary disorders, and pancreatitis, as clinically indicated.

Discontinue COBENFY in the presence of signs or symptoms of substantial liver injury such as jaundice, pruritus, or alanine aminotransferase levels more than five times the upper limit of normal or five times baseline values.

5.4 Decreased Gastrointestinal Motility

COBENFY contains trospium chloride. Trospium chloride, like other antimuscarinic agents, may decrease gastrointestinal motility. Administer COBENFY with caution in patients with gastrointestinal obstructive disorders because of the risk of gastric retention [see Contraindications (4)]. Use COBENFY with caution in patients with conditions such as ulcerative colitis, intestinal atony, and myasthenia gravis.

5.5 Risk of Angioedema

Angioedema of the face, lips, tongue, and/or larynx has been reported with COBENFY and trospium chloride, a component of COBENFY [see Adverse Reactions (6.2)]. In one case, angioedema occurred after the first dose of trospium chloride. Angioedema associated with upper airway swelling may be life-threatening. If involvement of the tongue, hypopharynx, or larynx occurs, discontinue COBENFY and initiate appropriate therapy and/or measures necessary to ensure a patent airway. COBENFY is contraindicated in patients with a history of hypersensitivity to trospium chloride.

5.6 Risk of Use in Patients with Narrow-angle Glaucoma

Pupillary dilation may occur due to the anticholinergic effects of COBENFY. This may trigger an acute angle closure attack in patients with anatomically narrow angles. In patients known to have anatomically narrow angles, COBENFY should only be used if the potential benefits outweigh the risks and with careful monitoring [see Contraindications (4)].

5.7 Increases in Heart Rate

COBENFY can increase heart rate [see Adverse Reactions (6.1)]. Assess heart rate at baseline and as clinically indicated during treatment with COBENFY [see Dosage and Administration (2.1)].

5.8 Anticholinergic Adverse Reactions in Patients with Renal Impairment

Trospium chloride, a component of COBENFY, is substantially excreted by the kidney. COBENFY is not recommended in patients with moderate or severe renal impairment (estimated glomerular filtration rate (eGFR) <60 mL/min). Systemic exposure of trospium chloride is higher in patients with moderate and severe renal impairment [see Use in Specific Populations (8.6) and Clinical Pharmacology (12.3)]. Therefore, anticholinergic adverse reactions (including dry mouth, constipation, dyspepsia, urinary tract infection, and urinary retention) are expected to be greater in patients with moderate and severe renal impairment.

5.9 Central Nervous System Effects

Trospium chloride, a component of COBENFY, is associated with anticholinergic central nervous system (CNS) effects [see Adverse Reactions (6.1)]. A variety of CNS anticholinergic effects have been reported with trospium chloride, including dizziness, confusion, hallucinations, and somnolence. Monitor patients for signs of anticholinergic CNS effects, particularly after beginning treatment or increasing the dose. Advise patients not to drive or operate heavy machinery until they know how COBENFY affects them. If a patient experiences anticholinergic CNS effects, consider dose reduction or drug discontinuation.

6 ADVERSE REACTIONS

The following clinically significant adverse reactions are described elsewhere in the labeling:

- Risk of Urinary Retention [see Warnings and Precautions (5.1)]
- Risk of Use in Patients with Hepatic Impairment [see Warnings and Precautions (5.2)]
- Risk of Use in Patients with Biliary Disease [see Warnings and Precautions (5.3)]
- Decreased Gastrointestinal Motility [see Warnings and Precautions (5.4)]
- Risk of Angioedema [see Warnings and Precautions (5.5)]
- Risk of Use in Patients with Narrow-angle Glaucoma [see Warnings and Precautions (5.6)]
- Increases in Heart Rate [see Warnings and Precautions (5.7)]
- Anticholinergic Adverse Reactions in Patients with Renal Impairment [see Warnings and Precautions (5.8)]
- Central Nervous System Effects [see Warnings and Precautions (5.9)]

6.1 Clinical Trials Experience

Because clinical trials are conducted under widely varying conditions, adverse reaction rates observed in the clinical trials of a drug cannot be directly compared to rates in the clinical trials of another drug and may not reflect the rates observed in practice.

COBENFY was evaluated for safety in a total of 1,594 subjects exposed to one or more doses, including 1,135 adult patients with schizophrenia and 389 healthy subjects. A total of 347 COBENFY-treated patients had at least 6 months of exposure and 150 patients had at least 1 year of exposure (defined as ≥ 50 weeks) from open-label studies.

The adverse reaction findings are based on two pooled 5-week, placebo-controlled, flexible-dose studies in 504 adult patients with schizophrenia in which COBENFY or placebo was started at an initial dose of 50 mg/20 mg twice daily for the first 2 days followed by 100 mg/20 mg twice daily for the remainder of Week 1 (Days 3 to 7). On Day 8, dosing was titrated to 125 mg/30 mg twice daily unless the patient could not tolerate it. All patients had the option to return to 100 mg/20 mg twice daily for the remainder of the treatment period [see Clinical Studies (14)].

In the 5-week placebo-controlled studies, 6% of patients treated with COBENFY and 4% of placebo-treated patients discontinued participation due to adverse reactions. Adverse reactions that led to study discontinuation in ≥1% of patients treated with COBENFY include nausea (2%) and vomiting (1%).

The most common adverse reactions (≥5% and at least twice placebo) were nausea, dyspepsia, constipation, vomiting, hypertension, abdominal pain, diarrhea, tachycardia, dizziness, and gastroesophageal reflux disease.

Adverse reactions reported with COBENFY at an incidence of at least 2% in patients exposed to COBENFY and greater than the rate of placebo are shown in Table 1.

Table 1: Adverse Reactions Reported in ≥2% of COBENFY-Treated Patients and Greater than Rate of Placebo in Two 5-week Schizophrenia Trials
 | COBENFY; (N=251) | Placebo; (N=253)
Nausea | 19% | 4%
Dyspepsiaa | 18% | 5%
Constipation | 17% | 7%
Vomiting | 15% | 1%
Hypertensionb | 11% | 2%
Abdominal Painc | 8% | 4%
Diarrhea | 6% | 2%
Tachycardiad | 5% | 2%
Dizziness | 5% | 2%
Gastroesophageal reflux disease | 5% | <1%
Dry mouth | 4% | 2%
Somnolence | 3% | 2%
Vision blurred | 3% | 0%
Salivary hypersecretion | 2% | 0%
Orthostatic hypotension | 2% | 1%
Coughe | 2% | 1%
Extrapyramidal symptoms (EPS), non-akathisiaf | 2% | <1%
a Dyspepsia includes dyspepsia, esophageal discomfort
b Hypertension includes hypertension, blood pressure increased, labile hypertension, orthostatic hypertension
c Abdominal Pain includes abdominal discomfort, abdominal pain upper, abdominal pain, abdominal pain lower, abdominal tenderness
d Tachycardia includes tachycardia, heart rate increased, sinus tachycardia
e Cough: includes cough, productive cough
f EPS (non-akathisia) includes dyskinesia, drooling, dystonia, extrapyramidal disorder, muscle contraction involuntary, muscle spasms

Increases in Heart Rate
In a dedicated 8-week clinical study, 24-hour ambulatory blood pressure monitoring (ABPM) was conducted in 133 patients with schizophrenia. A total of 95 patients had acceptable ABPM recordings at both baseline and Week 8. In that group, there was a mean change in 24-hour heart rate of 9.8 beats per minute (bpm) (95% CI 7.5, 12.2) from baseline to Week 8.

In the two placebo-controlled schizophrenia studies, COBENFY was associated with increases in heart rate compared to placebo, with peak elevation occurring on Day 8 of study treatment (13.5 bpm in the COBENFY group and 4.0 bpm in the placebo group), partially attenuating with continued dosing (11.4 bpm in the COBENFY group and 5.5 bpm in the placebo group at Week 5).

Liver Enzyme Elevations
In the 5-week, placebo-controlled schizophrenia studies, the proportions of patients with ALT or AST elevations of ≥3 times the upper limits of the normal reference range were 2.8% (6/214) for COBENFY-treated patients compared to 0.4% (1/224) of placebo-treated patients. Twenty-five (1.6%) of the total 1,594 subjects exposed to COBENFY had elevated liver enzymes. The majority of liver enzyme elevations occurred within the first month of treatment and resolved with continued COBENFY use, suggestive of liver adaptation; some cases required treatment interruption, and one was associated with an increase in bilirubin.

Urinary Retention
In the 5-week, placebo-controlled studies, urinary retention (urinary hesitation, dysuria, and urinary retention) was reported in 0.8% of COBENFY-treated patients and 0.4% on placebo. In the long-term, open-label studies, urinary retention was reported in 3.5% of COBENFY-treated patients. Urinary retention was more common in males, geriatric patients, and those with certain risk factors [see Warnings and Precautions (5.1)]. Urinary retention occurred at all doses but was predominately observed at the maximum COBENFY dose. In the long-term, open-label studies, urinary tract infections were reported in 2.3% of COBENFY-treated patients and were more commonly reported in females than males. Of the total 1,594 subjects exposed to COBENFY (including healthy volunteers and patients with schizophrenia or other conditions), four subjects required a Foley catheter, including one with elevated serum creatinine and one with urinary tract infections. Four subjects with urinary retention required reduction of COBENFY dose, four discontinued COBENFY, and four received medications for the treatment of benign prostatic hyperplasia (BPH).

6.2 Postmarketing Experience

The following adverse reactions have been identified during post-approval use of trospium chloride, one of the components of COBENFY. Because these reactions are reported voluntarily from a population of uncertain size, it is not always possible to reliably estimate their frequency or establish a causal relationship to drug exposure.

- Cardiovascular – chest pain, hypertensive crisis, palpitations, supraventricular tachycardia, syncope
- Gastrointestinal – gastritis
- General – rash
- Musculoskeletal – rhabdomyolysis
- Nervous System – confusion, delirium, dizziness, hallucinations, somnolence, vision abnormal
- Skin and subcutaneous tissue disorders – angioedema, anaphylactic reaction, Stevens-Johnson syndrome

7 DRUG INTERACTIONS

7.1 Clinically Significant Drug Interactions with COBENFY

Table 2 displays clinically significant drug interactions with COBENFY.

Table 2: Clinically Significant Drug Interactions with COBENFY
Strong Inhibitors of CYP2D6
Clinical Implication: | CYP2D6 contributes significantly to the metabolism of xanomeline, a component of COBENFY. Concomitant use of COBENFY with strong CYP2D6 inhibitors may increase plasma concentrations of xanomeline, which may increase the frequency and/or severity of adverse reactions from COBENFY [see Clinical Pharmacology (12.3)].
Prevention or Management: | Monitor patients for increased frequency and/or severity of adverse reactions related to COBENFY in patients taking COBENFY with strong inhibitors of CYP2D6.
Drugs Eliminated by Active Tubular Secretion
Clinical Implication: | Concomitant use of COBENFY with drugs that are eliminated by active tubular secretion may increase plasma concentrations of trospium a component of COBENFY, and/or the concomitantly used drug due to competition for this elimination pathway, which may increase the frequency and/or severity of adverse reactions from COBENFY or the drug eliminated by active tubular secretion [see Clinical Pharmacology (12.3)].
Prevention or Management: | Monitor patients for increased frequency and/or severity of adverse reactions related to COBENFY and adverse reactions related to drugs eliminated by active tubular secretion in patients concomitantly receiving such drugs.
Oral Drugs That Are Sensitive Substrates of CYP3A4
Clinical Implication: | Xanomeline, a component of COBENFY, transiently inhibits CYP3A4 locally in the gut but not systemically. Concomitant use of COBENFY with oral drugs that are sensitive substrates of CYP3A4 may result in increased plasma concentrations of the oral drugs that are sensitive substrates of CYP3A4. This may increase the frequency and/or severity of adverse reactions from such substrates [see Clinical Pharmacology (12.3)].
Prevention or Management: | Monitor patients for increased frequency and/or severity of adverse reactions related to oral drugs that are sensitive substrates of CYP3A4 in patients taking COBENFY with such substrates.
Oral Drugs That Are Substrates of P-glycoprotein
Clinical Implication: | Xanomeline, a component of COBENFY, transiently inhibits P-glycoprotein locally in the gut but not systemically. Concomitant use of COBENFY with oral drugs that are substrates of P-glycoprotein may result in increased plasma concentrations of the oral drugs that are substrates of P-glycoprotein, which may increase the frequency and/or severity of adverse reactions from such substrates [see Clinical Pharmacology (12.3)].
Prevention or Management: | Monitor patients for increased frequency and/or severity of adverse reactions related to oral drugs that are narrow therapeutic index substrates of P-glycoprotein in patients taking COBENFY with such substrates.

7.2 Other Antimuscarinic Drugs

Concomitant use of COBENFY with other antimuscarinic drugs that produce anticholinergic adverse reactions (e.g., dry mouth, constipation) may increase the frequency and/or severity of such effects. Monitor patients for increased frequency and/or severity of anticholinergic adverse reactions when COBENFY is used concomitantly with other antimuscarinic drugs.

7.3 Effects on Absorption of Drugs

COBENFY may potentially alter the absorption of some concomitantly administered drugs due to anticholinergic effects on gastrointestinal motility. Dosage adjustment of concomitant medications may be necessary based on clinical response and tolerability.

8 USE IN SPECIFIC POPULATIONS

8.1 Pregnancy

Pregnancy Exposure Registry
There is a pregnancy exposure registry that monitors outcomes in women exposed to psychiatric medications, including COBENFY, during pregnancy. Healthcare providers are encouraged to advise patients to register by calling 1-866-961-2388 or visiting online at https://womensmentalhealth.org/research/pregnancyregistry/atypicalantipsychotic/.

Risk Summary
There are no available data on COBENFY use in pregnant women to evaluate for a drug-associated risk of major birth defects, miscarriage or other adverse maternal or fetal outcomes. There are risks to the mother associated with untreated schizophrenia (see Clinical Considerations). In animal reproduction studies, oral administration of xanomeline alone or in combination with trospium chloride during the period of organogenesis or during pregnancy and lactation caused maternal toxicities of adverse clinical signs, decreased body weight, weight gain and food consumption, and/or maternal death. At these maternally toxic doses, embryofetal and developmental toxicities included decreased fetal and neonatal weight, stillborn pups, and/or neonatal deaths. The no observed adverse effect level (NOAEL) of xanomeline or xanomeline/trospium chloride combination for maternal, embryofetal, and/or developmental toxicity is equal to or higher than the xanomeline and trospium chloride dose at the maximum recommended human dose (MRHD) of 250/60 mg xanomeline/trospium chloride, based on mg/m^2 body surface area (BSA) (see Data).

The background risk of major birth defects and miscarriage for the indicated population is unknown. All pregnancies have a background risk of major birth defect, loss, or other adverse outcomes. In the U.S. general population, the estimated background risk of major birth defects and miscarriage in clinically recognized pregnancies is 2% to 4% and 15% to 20%, respectively.

Clinical Considerations
Disease-associated maternal and/or embryofetal risk
There is a risk to the pregnant patient from untreated schizophrenia, including increased risk of relapse, hospitalization, and suicide. Schizophrenia is associated with adverse perinatal outcomes, including preterm birth. It is not known if this is a direct result of the illness or other comorbid factors.

Data

Animal Data
Pregnant rats were orally treated during the period of organogenesis with 150 mg/kg/day xanomeline alone, 100 mg/kg/day trospium chloride alone, or xanomeline/trospium chloride combination at 30/25, 75/50, and 150/100 mg/kg/day, respectively. Xanomeline alone and the high dose combination caused maternal toxicities of decreased body weight, weight gain, and food consumption. At these maternally toxic doses, fetal weights were decreased. The NOAEL for maternal and embryofetal toxicity is 75/50 mg/kg/day for the combination, which is approximately 3 and 8 times the xanomeline and trospium chloride dose, respectively, at the MRHD of 250/60 mg xanomeline/trospium chloride, based on BSA. No fetal malformation was observed. Trospium chloride alone did not cause maternal or embryofetal toxicity.

Pregnant rabbits were orally treated during the period of organogenesis with120 mg/kg/day xanomeline alone, 80 mg/kg/day trospium chloride alone, or xanomeline/trospium chloride combination at 30/20, 60/40, and 120/80 mg/kg/day, respectively. Xanomeline alone and the high dose combination caused maternal toxicities of decreased body weight, weight gain, and food consumption, and/or early abortion. At these maternally toxic doses, decreased fetal weight and decreased fetal viability (increased resorption and post-implantation loss) were observed. The NOAEL for maternal and embryofetal toxicity is 60/40 mg/kg/day for the xanomeline/trospium chloride combination, which is 5 and 13 times the xanomeline and trospium chloride dose, respectively at the MRHD, based on BSA. No fetal malformation was observed. Trospium chloride alone did not cause maternal or embryofetal toxicity.

Rats were orally treated during pregnancy and lactation with 30, 75, and 150 mg/kg/day xanomeline alone, 100 mg/kg/day trospium chloride alone, or xanomeline/trospium chloride combination at 30/25, 75/50, and 150/100 mg/kg/day, respectively. Xanomeline alone at ≥ 75 mg/kg/day or in combination with trospium chloride at ≥ 75/50 mg/kg/day caused maternal toxicity of adverse clinical signs, decreased body weight, weight gain, food consumption, and maternal death. At these maternally toxic doses, developmental toxicity was observed in the offspring, including growth suppression (decreased body weight and weight gain), delayed developmental landmarks, stillborn pups, and neonatal deaths. No drug effect was observed on the neurobehavioral function, including learning and memory, or the reproductive capacity of the offspring. The NOAEL for maternal and developmental toxicity is 30/25 mg/kg/day for the xanomeline/trospium chloride combination, which is approximately 1 and 4 times the xanomeline and trospium chloride dose, respectively at the MRHD, based on BSA. Trospium chloride alone did not cause maternal or developmental toxicity.

Pregnant rats were treated during the period of organogenesis with trospium chloride at doses up to 200 mg/kg/day. No malformation or fetal toxicity was observed up to 200 mg/kg/day, which is approximately 32 times the trospium chloride dose at the MRHD of 250/60 mg xanomeline/trospium chloride based on BSA.

Pregnant rabbits were treated during the period of organogenesis with trospium chloride at doses up to 200 mg/kg/day. Maternal toxicity (reduced feces, hunched posture, and diarrhea) was observed at 200 mg/kg/day. The NOAEL for maternal toxicity is 20 mg/kg/day, which is approximately 3 times the trospium chloride dose at the MRHD based on BSA.

Rats were orally treated during pregnancy and lactation with trospium chloride at doses up to 200 mg/kg/day. Maternal toxicity (death, irregular breathing, increased excitability) and neonatal deaths were observed at 200 mg/kg/day, which is approximately 32 times the MRHD, based on BSA. The NOAEL for maternal and developmental toxicity is 20 mg/kg/day, which is approximately 3 times the trospium chloride dose at the MRHD, based BSA.

8.2 Lactation

Risk Summary
There are no data on the presence of xanomeline or trospium in human milk, the effects on the breastfed infant, or the effects on milk production. Xanomeline and trospium are present in animal milk. When a drug is present in animal milk, it is likely that the drug will be present in human milk. The developmental and health benefits of breastfeeding should be considered along with the mother’s clinical need for COBENFY and any potential adverse effects on the breastfed infant from COBENFY or from the underlying maternal condition.

8.4 Pediatric Use

The safety and effectiveness of COBENFY in pediatric patients have not been established.

8.5 Geriatric Use

Controlled clinical studies of COBENFY did not include patients older than 65 years of age to determine whether they respond differently from younger adult patients.

Because COBENFY can increase the risk of urinary retention in geriatric patients, including older males with bladder outlet obstruction due to benign prostatic hyperplasia (BPH), a slower titration and lower maximum dosage is recommended in geriatric patients [see Dosage and Administration (2.3) and Warnings and Precautions (5.1)].

8.6 Renal Impairment

Patients with mild renal impairment (eGFR 60 to <90 mL/min) showed higher systemic exposures to trospium chloride and xanomeline, the components of COBENFY, compared to subjects with normal renal function. However, in the adequate and well-controlled clinical studies, the safety profiles in patients with mild renal impairment were similar to those observed in patients with normal renal function (eGFR ≥90 mL/min). Therefore, the recommended dosage in patients with mild renal impairment is the same as the recommended dosage for patients with normal renal function.

Use of COBENFY is not recommended in patients with moderate or severe renal impairment (eGFR<60 mL/min) [see Warnings and Precautions (5.1, 5.8) and Clinical Pharmacology (12.3)].

8.7 Hepatic Impairment

Patients with mild to moderate hepatic impairment (Child-Pugh Class A and B, respectively) have higher xanomeline exposures compared to patients with normal hepatic function [see Clinical Pharmacology (12.3)]. The pharmacokinetics of COBENFY were not studied in patients with severe hepatic impairment (Child-Pugh Class C).

Use of COBENFY is contraindicated in patients moderate or severe hepatic impairment [see Contraindications (4) and Warnings and Precautions (5.2)]. It is not recommended in patients with mild hepatic impairment.

10 OVERDOSAGE

Overdose of COBENFY may produce cholinergic, anticholinergic or a combination of cholinergic and anticholinergic signs and symptoms:

- Cholinergic Signs and Symptoms: seizures, vomiting, diarrhea, abdominal pain, hyperhidrosis, salivary hypersecretion, and hypotension possibly preceded by hypertension.
- Anticholinergic Signs and Symptoms (geriatric patients may be more susceptible): delirium, agitation, garbled speech, dizziness, hypertension, tachycardia, dry mouth and eyes, ileus, blurred vision, and urinary retention.

Consider calling the Poison Help Line 1-800-222-1222 or a medical toxicologist for specific treatment recommendations.

11 DESCRIPTION

COBENFY is a combination of xanomeline, a muscarinic agonist, and trospium chloride, a muscarinic antagonist.

The chemical name of xanomeline tartrate is pyridine, 3-[4-(hexyloxy)-1,2,5-thiadiazol-3-yl]-1,2,5,6-tetrahydro-1-methyl-, (2R,3R)-2,3-dihydroxybutanedioate (1:1). Its molecular formula is C14H23N3OS.C4H6O6 and its molecular weight is 431.51 g/mol. Xanomeline tartrate is a white to slightly tan crystalline solid. Xanomeline tartrate is highly soluble in protic solvents, such as methanol and water, and in polar organic solvents such as DMF and dimethyl sulfoxide (DMSO). It is poorly soluble in lipophilic organic solvents, such as hexane or octanol.

The chemical structure of xanomeline tartrate is:

Trospium chloride is a quaternary ammonium compound with the chemical name of spiro[8-azoniabicyclo[3.2.1]octane-8,1′-pyrrolidinium], 3-[(2-hydroxy-2,2-diphenylacetyl)oxy]-, chloride (1:1), (1α,3β,5α). The molecular formula of trospium chloride is C25H30NO3.Cl and its molecular weight is 427.96 g/mol. Trospium chloride is a fine, colorless to slightly yellow, crystalline solid. Trospium chloride is highly soluble in water, freely soluble in methanol, and practically insoluble in methylene chloride.

The chemical structure of trospium chloride is:

COBENFY (xanomeline and trospium chloride) is for oral administration and is available in capsules in the following strengths:

- 50 mg/20 mg (equivalent to 76.7 mg xanomeline tartrate and 18.3 mg trospium).
- 100 mg/20 mg (equivalent to 153.3 mg xanomeline tartrate and 18.3 mg trospium).
- 125 mg/30 mg (equivalent to 191.7 mg xanomeline tartrate and 27.5 mg trospium).

COBENFY capsules contain a combination of pellets of xanomeline and pellets of trospium chloride.

Inactive ingredients: The xanomeline tartrate pellets contain ascorbic acid, microcrystalline cellulose, and talc.

The trospium chloride pellets contain lactose monohydrate, microcrystalline cellulose, and talc.

The capsules, printed with black ink, contain black iron oxide (only 100 mg/20 mg), hypromellose, red iron oxide, titanium dioxide, and yellow iron oxide (only 50 mg/20 mg and 100 mg/20 mg).

12 CLINICAL PHARMACOLOGY

12.1 Mechanism of Action

The mechanism of action of xanomeline in the treatment of schizophrenia is unclear; however, its efficacy is thought to be due to its agonist activity at M1 and M4 muscarinic acetylcholine receptors in the central nervous system.

Trospium chloride is a muscarinic antagonist. Trospium chloride antagonizes the muscarinic receptors primarily in the peripheral tissues.

12.2 Pharmacodynamics

Xanomeline binds to muscarinic receptors M1 to M5 with comparable affinity (Ki=10, 12, 17, 7, and 22 nM for the M1, M2, M3, M4, and M5 receptors, respectively) and exhibits higher agonist activity at the M1 and M4 receptors.

Trospium chloride antagonizes the muscarinic receptors primarily in peripheral tissues.

Cardiac Electrophysiology
At the maximum recommended dosage of 125 mg/30 mg twice daily, COBENFY does not prolong the QT interval to any clinically relevant extent.

12.3 Pharmacokinetics

Following COBENFY administration, xanomeline area under the plasma concentration-time curve during a 12-hour dosing interval (AUC0-12) at steady state and maximum concentration (Cmax) increased 50% when the COBENFY dose increased from 100 mg/20 mg twice daily to 125 mg/30 mg twice daily. Trospium exposures increase dose-proportionally over the COBENFY dosage range of 100 mg/20 mg twice daily to 125 mg/30 mg twice daily.

Pharmacokinetic properties of COBENFY are provided in Table 3.

Table 3: Pharmacokinetic Properties of COBENFY
Parameter |  | Xanomeline | Trospium
General Information
Dose proportionality |  | Greater than proportional | Proportional
Accumulationa |  | 2 to 3-fold | 2 to 3-fold
Time to steady state |  | 3 to 5 days | 3 to 5 days
Absorption
Tmax |  | 2 hours | 1 hour
Effect of food: PK in fed state (compared to fasted state)
High fat mealb | Cmax | Unchanged | Reduced 70% to 75%
High fat mealb | AUC | Increased 30% | Reduced 85% to 90%
Low fat mealb | Cmax | Unchanged | Reduced 70% to 75%
Low fat mealb | AUC | Unchanged | Reduced 85% to 90%
Distribution
Central volume of distribution (oral) |  | 10,800 Liters | 531 Liters
Plasma protein binding |  | Approximately 95% | Approximately 80%
Elimination
Half-life (t1/2) |  | 5 hours | 6 hours
Apparent clearance |  | 1950 Liters/hour | 796 Liters/hour
Renal clearance |  | 0.085 Liters/hour | 21 Liters/hour
Metabolism
Primary metabolic pathways | CYP450 | 2D6, 2B6, 1A2, 2C9, and 2C19 | Unlikely
Primary metabolic pathways | Other | Flavin monooxygenases (FMO1 and FMO3) | Ester hydrolysis and glucuronic acid conjugation; (not fully characterized)
Excretion
Urine | Total | 78% | Unknown
Urine | Unchanged | Less than 0.01% | 85-90%
Urine | Tubular secretion | Unknown | Yes
Feces | Total | 12% | Unknown
Feces | Unchanged | Unknown | Unknown
Abbreviations: AUC = Area under the time-concentration curve; Cmax = Maximum concentration; Tmax =Time to Cmax
a Dose-normalized accumulation at steady state
b High-fat high-calorie meal is 800-1000 calories, 50% from fat; a low-fat meal is 400-500 calories, 25% from fat

Specific Populations

Geriatric Patients
Population pharmacokinetic analysis suggests that AUC0-12h and Cmax of trospium at steady state were 60% higher and 36% higher, respectively, in subjects 65 years and older compared to subjects younger than 65 years old. The exposures (AUC0-12h and Cmax) of xanomeline at steady state were not different between subjects 65 years and older and subjects younger than 65 years old [see Dosage and Administration (2.3) and Use in Specific Populations (8.5)].

Male and Female Patients
Plasma concentrations of xanomeline and trospium are similar between females and males.

Racial or Ethnic Groups
Most subjects in clinical studies were Black.
Xanomeline and trospium exposure did not differ between Black and non-Black subjects. Studies have included too few subjects of Asian descent to evaluate comparisons.

Patients with Renal Impairment
The effect of renal impairment on xanomeline and trospium exposure was assessed in a dedicated study that enrolled healthy subjects and subjects with mild, moderate, or severe renal impairment. Estimated glomerular filtration rate (eGFR) was determined by the MDRD equation.

Plasma concentrations of xanomeline and trospium increased with increasing renal dysfunction [see Use in Specific Populations (8.6)]. For xanomeline, compared to subjects with normal renal function (eGFR: ≥90 mL/min), the steady-state Cmax and AUC0-12h were 2.1 and 1.9 times higher in subjects with mild renal impairment (eGFR: 60 to <90 mL/min), 2.4 and 2.1 times higher in subjects with moderate renal impairment (eGFR: 30 to <60 mL/min), and 2.6 and 2.4 times higher in subjects with severe renal impairment (eGFR: <30 mL/min). For trospium, compared to subjects with normal renal function, the steady-state Cmax and AUC0-12h were 1.6 and 1.6 times higher in subjects with mild renal impairment, 2.7 and 2.2 times higher in subjects with moderate renal impairment, and 2.9 and 2.9 times higher in subjects with severe renal impairment.

Patients with Hepatic Impairment
The effect of hepatic impairment on xanomeline and trospium in combination was assessed in a dedicated study that enrolled healthy subjects and subjects with mild or moderate hepatic impairment as determined by their Child-Pugh score.

Plasma concentrations of xanomeline increased with increasing hepatic dysfunction [see Use in Specific Populations (8.7)]. In subjects with mild hepatic impairment (Child-Pugh Class A), the steady-state Cmax and AUC0-12h of xanomeline was 2.8 and 2.6 times that in subjects with normal hepatic function. Mild and moderate hepatic impairment did not substantially affect trospium exposure, but significantly impacted xanomeline exposures. In subjects with moderate hepatic impairment (Child-Pugh Class B), the steady-state Cmax and AUC0-12h of xanomeline was at least 7 times that in subjects with normal hepatic function [see Contraindications (4) and Warnings and Precautions (5.2)].

The effect of severe hepatic impairment on xanomeline and trospium exposure was not evaluated.

Body Weight
Compared to subjects weighing 70 kg, xanomeline exposures were 30 to 35% lower and trospium exposures were 20 to 35% lower in subjects weighing 120 kg. The lower exposures observed in subjects weighing 120 kg are expected to be clinically not meaningful.

Drug Interaction Studies
Drugs Eliminated by Active Tubular Secretion

Active tubular excretion is a major elimination pathway for trospium. Trospium has the potential for pharmacokinetic interactions with other drugs that are eliminated by active tubular secretion. Coadministration of COBENFY with these drugs may increase plasma concentrations of trospium and/or the coadministered drug due to competition for this elimination pathway [see Drug Interactions (7.1)].

Metformin
A drug interaction study was conducted in which extended-release trospium chloride 60 mg once daily was coadministered with metformin hydrochloride 500 mg twice daily under steady-state conditions in 44 healthy subjects. Co-administration of 500 mg metformin immediate-release tablets twice daily reduced the steady-state systemic exposure of trospium by approximately 29% for mean AUC0-24 and by 34% for mean Cmax. The steady-state pharmacokinetics of metformin were comparable when administered with or without 60 mg extended-release trospium chloride once daily under fasted conditions. The effect of metformin at higher doses on trospium pharmacokinetics is unknown.

Drugs That Inhibit CYP2D6
CYP2D6 is a significant contributor to the metabolism of xanomeline. Drugs that are inhibitors of CYP2D6 may increase xanomeline concentrations in plasma [see Drug Interactions (7.1)].

Drugs That Are Substrates of P-glycoprotein
In vitro data suggest that xanomeline does not inhibit P-glycoprotein systemically, but it may transiently inhibit P-glycoprotein locally in the intestine after dosing. COBENFY may increase plasma concentrations of coadministered P-gp substrates [see Drug Interactions (7.1)].

Drugs That Are Substrates of CYP3A4
In vitro data suggest that xanomeline does not inhibit CYP3A4 systemically, but it may transiently inhibit CYP3A4 locally in the intestine after dosing. COBENFY may increase plasma concentrations of coadministered CYP3A4 substrates [see Drug Interactions (7.1)].

12.5 Pharmacogenomics

CYP2D6 is a significant contributor to the metabolism of xanomeline. The gene encoding CYP2D6 has polymorphisms that impact protein function. Based on a population pharmacokinetic analysis, compared to subjects with normal CYP2D6 function, the median Cmax and median AUC0-12h of xanomeline were estimated to increase by 28% and 15% in CYP2D6 intermediate metabolizers (N=84) and decrease by 43% in both parameters for ultrarapid metabolizers (N=12). The pharmacokinetics of xanomeline have not been adequately characterized in subjects who are poor metabolizers.

13 NONCLINICAL TOXICOLOGY

13.1 Carcinogenesis, Mutagenesis, Impairment of Fertility

Carcinogenesis

Xanomeline
Xanomeline was administered to rats in the diet at doses of 9, 37, and 134 mg/kg/day in males and 11, 46, and 170 mg/kg/day in females, respectively, for two years. Biliary hyperplasia was observed in all groups with increased incidence and/or severity at ≥ 37 and 46 mg/kg/day in males and females, respectively, relative to controls. There was no increase in the incidence of tumors at doses up to 37 and 46/mg/kg/day in males and females, respectively; these doses are 1.4 to 1.8 times higher than the xanomeline dose at the MRHD of 250/60 mg xanomeline/trospium, based on mg/m^2 BSA. The high doses of 134 and 170 mg/kg/day in males and females exceeded the maximum tolerated dose (MTD), precluding an adequate assessment for carcinogenic effect at this dose.

Xanomeline was administered to mice in the diet at doses of 52, 174, and 559 mg/kg/day for 21 months in both sexes. Xanomeline did not increase the incidence of tumors in mice at doses up to 174 mg/kg/day, which is approximately 3 times the xanomeline dose at the MRHD, based on BSA. The high dose of 559 mg/kg/day exceeded the MTD, precluding an adequate assessment for carcinogenic effect at this dose.

Trospium chloride
Trospium chloride did not increase the incidence of tumors in rats treated for 104 weeks at doses up to 200 mg/kg/day, which is approximately 32 times the trospium chloride dose at the MRHD, based on BSA.

Trospium chloride did not increase the incidence of tumors in mice treated for 78 weeks at doses up to 200 mg/kg/day, which is approximately 16 times the trospium chloride dose at the MRHD, based on BSA.

Mutagenesis

Xanomeline
Xanomeline was not mutagenic in the in vitro bacterial reverse mutation (Ames assay) or mouse lymphoma assay. Xanomeline did not induce unscheduled DNA synthesis in rat hepatocytes and was not clastogenic in the in vitro chromosome aberration assay or in the in vivo mouse bone marrow micronucleus assay.

Trospium chloride
Trospium chloride was not mutagenic nor genotoxic in tests in vitro in bacteria (Ames assay) and mammalian cells (L5178Y mouse lymphoma and CHO cells) or in vivo in the rat micronucleus test.

Impairment of Fertility

Xanomeline
Xanomeline did not affect fertility when orally administered to male rats via the diet at doses of 15, 44, and 150 mg/kg/day. The NOAEL for male fertility is 150 mg/kg/day, which is approximately 6 times the xanomeline dose at the MRHD of 250/60 mg xanomeline/trospium, based on BSA.

Xanomeline did not affect fertility when administered subcutaneously to male and female rats at doses of 1, 5, and 25 mg/kg/day. The NOAEL for male and female fertility is 25 mg/kg/day, which is equal to the xanomeline dose at the MRHD, based on BSA.

Trospium chloride
Trospium chloride did not affect fertility in rats at doses up to 200 mg/kg/day which is approximately 32 times the trospium chloride dose at the MRHD, based on BSA.

13.2 Animal Toxicology and/or Pharmacology

In the 2-year dietary study in rats, biliary cysts and/or biliary/biliary ductule dilatation were observed at xanomeline doses equal to or greater than the MRHD of 250/60 mg xanomeline/trospium chloride, based on BSA.

14 CLINICAL STUDIES

The efficacy of COBENFY for the treatment of schizophrenia in adults was evaluated in two placebo-controlled studies with identical designs (N = 470). Study 1 (NCT04659161) and Study 2 (NCT04738123) were five-week, randomized, double-blind, placebo-controlled, multi-center studies in adult patients with a diagnosis of schizophrenia according to the DSM-5 criteria.

In Study 1 and Study 2, patients randomized to COBENFY were started on an initial dose of 50 mg/20 mg orally twice daily for the first 2 days and if tolerated, followed by 100 mg/20 mg orally twice daily for the remainder of Week 1 (Days 3 to 7). On Day 8, dosing was titrated upwards to 125 mg/30 mg orally twice daily unless the patient could not tolerate it. All patients could return to 100 mg/20 mg orally twice daily for the remainder of the treatment period.

Demographic and baseline disease characteristics were similar for the COBENFY and placebo groups. Median age was 46 years (range 19 to 65 years). Twenty-five percent of patients were female, 31% were White, 68% were Black or African American, and 1% were Other (or not reported).

The primary efficacy measure was the change from baseline in the Positive and Negative Syndrome Scale (PANSS) total score at Week 5. The PANSS is a 30-item scale that measures symptoms of schizophrenia. Each item is rated by a clinician on a seven-point scale. A score of 1 indicates the absence of symptoms, and a score of 7 indicates extremely severe symptoms. The PANSS total score may range from 30 to 210 with higher scores reflecting greater overall symptom severity.

In Study 1 and Study 2, patients randomized to COBENFY showed a statistically significant reduction from baseline to Week 5 in the PANSS Total Score compared to the placebo group. The results of Studies 1 and 2 are shown in Table 4. A secondary endpoint, the change from baseline to Week 5 on the Clinical Global Impression‒Severity (CGI-S) score, was statistically significant for COBENFY compared to placebo in Study 1. The CGI-S is a validated clinician-rated scale that measures the patient’s current illness state and overall clinical state on a 1 (normal, not at all ill) to 7-point (extremely ill) scale.

Examination of subgroups by age, sex, and race did not suggest differences in response in the study (there were no patients over 65 years of age).

Table 4: Primary Efficacy Results for Change from Baseline in PANSS Total Score at Week 5 in Adults with Schizophrenia (Studies 1 and 2)
 |  |  | Primary Efficacy Endpoint: PANSS Total Score
Study Number | Treatment Group | N | Mean Baseline Score (SD) | LS Mean Change from Baseline (SE) | Placebo-subtracted Difference; (95% CI) a
1 | COBENFY | 117 | 98.2 (8.9) | -21.2 (1.7) | -9.6 (-13.9, -5.2)*
1 | Placebo | 119 | 97.7 (9.4) | -11.6 (1.6)
2 | COBENFY | 114 | 96.9 (8.8) | -20.6 (1.6) | -8.4 (-12.4, -4.3)*
2 | Placebo | 120 | 96.5 (8.8) | -12.2 (1.6)

The PANSS Total Score may range from 30 to 210; higher scores reflect greater symptom severity.

SD: standard deviation; SE: standard error; LS Mean: least-squares mean; CI: confidence interval.

a Difference (drug minus placebo) in LS mean change from baseline.

*Statistically significantly superior to placebo.

The change from baseline in PANSS total score to Week 5 is summarized in Figure 1.

Figure 1: Change from Baseline in PANSS Total Score by Week in Adults with Schizophrenia (Study 1)

Error bars represent standard error. LS=least squares; SE=standard error

16 HOW SUPPLIED/STORAGE AND HANDLING

How Supplied

COBENFY is available as:

- 50 mg/20 mg (xanomeline/trospium chloride): Buff capsules imprinted with Karuna 50/20 mg
- 100 mg/20 mg (xanomeline/trospium chloride): Brown capsules imprinted with Karuna 100/20 mg
- 125 mg/30 mg (xanomeline/trospium chloride): Swedish Orange capsules imprinted with Karuna 125/30 mg

COBENFY capsules are packaged as described in Table 5.

Table 5: COBENFY Packaging Configurations
Capsule Strength | Total Package Count | Package Configuration | Package Components | NDC Code
50 mg/20 mg | 60 | Bottle | N/A | 0003-0050-60
50 mg/20 mg | 100 | Hospital Unit-Dose Blister | 10 Blister Cards with 10 Capsules Each | 0003-0050-98
100 mg/20 mg | 60 | Bottle | N/A | 0003-1100-60
100 mg/20 mg | 100 | Hospital Unit-Dose Blister | 10 Blister Cards with 10 Capsules Each | 0003-1100-98
125 mg/30 mg | 60 | Bottle | N/A | 0003-0125-60
125 mg/30 mg | 100 | Hospital Unit-Dose Blister | 10 Blister Cards with 10 Capsules Each | 0003-0125-98
50 mg/20 mg (4); 100 mg/20 mg (52) | 56 | Starter Pack for 100 mg/20 mg dose | 1 Mixed Blister Wallet: four (4) 50 mg/20 mg capsules and ten (10) 100 mg/20 mg capsules; and; 3 Wallets: fourteen (14) 100 mg/20 mg capsules in each wallet | 0003-5200-56

Storage and Handling

Store at 20°C to 25°C (68°F to 77°F); excursions permitted to 15°C to 30°C (59°F to 86°F) [see USP Controlled Room Temperature].

17 PATIENT COUNSELING INFORMATION

Advise the patient to read the FDA-approved patient labeling (Patient Information).

Risk of Urinary Retention
Inform patients that COBENFY may cause urinary retention and that the risk of urinary retention is greater in some patients, including geriatric patients and those with bladder outlet obstruction (e.g., due to BPH) and patients with other causes of reduced bladder emptying (e.g., diabetic cystopathy). Urinary retention may occur at any time during treatment with COBENFY and is more likely when taking higher doses.

Advise patients to monitor for symptoms of urinary retention, such as urinary hesitancy, weak urinary stream, incomplete bladder emptying and pain with urination, and to promptly report these symptoms to their healthcare provider. Inform patients that urinary retention may increase the risk of urinary tract infection. Advise patients to seek immediate medical attention if they are unable to urinate [see Warnings and Precautions (5.1)].

Risk of Use in Patients with Hepatic Impairment
Instruct patients to report signs of hepatic impairment (e.g., skin and eyes that appear yellowish, abdominal pain and swelling, itchy skin, dark urine color) and symptoms of hepatic injury (e.g., biliary spasm, pancreatitis, and cholangitis) to their healthcare provider [see Warnings and Precautions (5.2)].

Risk of Use in Patients with Biliary Disease
Inform patients that COBENFY can increase liver enzymes and about the need for specific monitoring, including liver enzymes and bilirubin levels. Inform patients to report symptoms such as dyspepsia, nausea, vomiting, or upper abdominal pain to their healthcare provider [see Warnings and Precautions (5.3)].

Decreased Gastrointestinal Motility
Inform patients that COBENFY can delay or slow emptying of food in their stomach. Advise patients to inform their healthcare provider about the presence of or symptoms of gastrointestinal obstructive disorders and conditions such as ulcerative colitis, intestinal atony, and myasthenia gravis [see Warnings and Precautions (5.4)].

Risk of Angioedema
Advise patients that hypersensitivity reactions to COBENFY could and occur and result in life-threatening airway obstruction. Instruct patients to seek medical attention if they experience edema of the tongue, edema of the laryngopharynx, or difficulty breathing occurs, discontinue COBENFY, and seek immediate medical attention [see Warnings and Precautions (5.5)].

Risk of Use in Patients with Narrow-angle Glaucoma
Inform patients pupillary dilation may occur with COBENFY use and in susceptible individuals, can lead to an episode of angle closure glaucoma [see Warnings and Precautions (5.6)].

Increases in Heart Rate
Inform patients that COBENFY can increase heart rate [see Warnings and Precautions (5.7)].

Anticholinergic Adverse Reactions in Patients with Renal Impairment
Inform patients that COBENFY is associated with anticholinergic adverse reactions such as dry mouth, constipation, dyspepsia, urinary tract infection, and urinary retention and the effects are expected to be greater in patients with renal impairment [see Warnings and Precautions (5.8)].

Central Nervous System Effects
Advise patients that COBENFY is associated with central nervous system effects such as dizziness, confusion, hallucinations, and somnolence. Caution patients about performing activities requiring mental alertness, such as operating hazardous machinery or operating a motor vehicle, until they are reasonably certain that COBENFY therapy does not adversely affect their ability to engage in such activities [see Warnings and Precautions (5.9)].

Administration Information
Instruct patients to take COBENFY twice daily at least one hour before a meal or at least 2 hours after a meal and not to open the capsules [see Dosage and Administration (2.2)].

Concomitant Medications
Advise patients to inform their health care providers of any changes to their current prescription or over-the-counter medications because there may be a potential for interactions [see Drug Interactions (7)].

Pregnancy
Advise patients to notify their healthcare provider with a known or suspected pregnancy. Advise pregnant women that there is a pregnancy exposure registry that monitors outcomes in females exposed to COBENFY during pregnancy [see Use in Specific Populations (8.1)].

Marketed by:
Bristol-Myers Squibb Company
Princeton, NJ 08543 USA
COBENFY is a trademark of Karuna Therapeutics, Inc., a Bristol Myers Squibb company.

PATIENT INFORMATION
COBENFY™ (co-BEN-fee)
(xanomeline and trospium chloride)
capsules

What is COBENFY?
COBENFY is a prescription medicine used to treat schizophrenia in adults.

It is not known if COBENFY is safe and effective in children.

Do not take COBENFY if you:

- have urinary retention problems that cause your bladder to not empty completely or not empty at all
- have moderate or severe liver problems (impairment)
- have gastric retention problems that cause your stomach to empty slowly
- are allergic to COBENFY, xanomeline, or trospium chloride, or any of the ingredients in COBENFY. See the end of this Patient Information leaflet for a complete list of ingredients in COBENFY.
- have an eye problem called untreated narrow-angle glaucoma

Before taking COBENFY, tell your healthcare provider about all of your medical conditions, including if you:

- have an enlarged prostate, problems passing urine, or a blockage in your urinary bladder
- have liver problems
- have or had gallstones or problems with your bile ducts or pancreas
- have stomach or intestinal problems including constipation, ulcerative colitis, slow emptying of your stomach, or myasthenia gravis
- have an eye condition called narrow-angle glaucoma
- have kidney problems
- are pregnant or plan to become pregnant. It is not known if COBENFY may harm your unborn baby. Tell your healthcare provider if you become pregnant or think you are pregnant during treatment with COBENFY.
  - There is a pregnancy exposure registry for women who take COBENFY during pregnancy. The purpose of this registry is to collect information about the health of women exposed to COBENFY and their baby. If you become pregnant during treatment with COBENFY, your healthcare provider will register you by calling 1-866-961-2388 or online at https://womensmentalhealth.org/research/pregnancyregistry/atypicalantipsychotic/.
- are breastfeeding or plan to breastfeed. It is not known if COBENFY passes into your breast milk or if it can harm your baby.

Tell your healthcare provider about all the medicines you take, including prescription and over-the-counter medicines, vitamins, and herbal supplements. Taking COBENFY with certain other medicines may increase your risk of side effects from COBENFY or the other medicine and may affect the way COBENFY or the other medicine works. Know the medicines you take. Keep a list of them to show your healthcare provider and pharmacist when you get a new medicine.

How should I take COBENFY?

- Take COBENFY exactly as your healthcare provider tells you. Do not change the dose or stop taking COBENFY without first talking to your healthcare provider.
- Take 1 COBENFY capsule 2 times each day.
- Take COBENFY by mouth at least 1 hour before a meal or at least 2 hours after a meal.
- Do not open the capsules.
- If you take too much COBENFY, call your healthcare provider or Poison Help Line at 1-800-222-1222, or go to the nearest hospital emergency room right away.

What should I avoid while taking COBENFY?

Do not drive, operate heavy machinery, or do other dangerous activities until you know how COBENFY affects you. COBENFY may cause dizziness, confusion, seeing or hearing things that are not real (hallucinations), and sleepiness.

What are the possible side effects of COBENFY?

COBENFY may cause serious side effects, including:

- Problems with emptying your bladder (urinary retention). See “Do not take COBENFY if you:” COBENFY may cause your bladder to not empty completely or not empty at all. You are at increased risk for urinary retention if you are elderly, have a blockage in your bladder, have an enlarged prostate called benign prostatic hyperplasia (BPH), have bladder emptying problems from diabetes, or are taking higher doses of COBENFY. Urinary retention may increase your risk for getting a urinary tract infection. Call your healthcare provider or get emergency help right away if you get any signs or symptoms of urinary retention during treatment with COBENFY, including:

- difficulty urinating
- urination in a weak stream or drips
- urinating frequently

- full bladder and difficulty emptying your bladder
- pain when you urinate

- Risks in people with liver problems. See “Do not take COBENFY if you:” It is not recommended that people with mild liver problems (impairment) take COBENFY because they have an increased risk of getting side effects from COBENFY. Your healthcare provider will check the liver enzyme levels in your blood before starting treatment and as needed during treatment with COBENFY. Tell your healthcare provider if you get any signs or symptoms of liver problems during treatment with COBENFY, including:

- yellowing of your skin or the white part of your eyes
- dark urine
- pain and swelling in the upper right part of your stomach (abdomen)
- stomach pain that spreads to your back or to below your right shoulder
- itching

- nausea or vomiting
- loss of appetite
- fever
- chills
- light colored stools
- tiredness

- Risks in people with bile duct and gallbladder problems (biliary disease). COBENFY may cause a blockage in your bile ducts that could lead to gallstones, pancreatitis, and increases in your liver enzymes. Your healthcare provider will check your liver enzyme and bilirubin levels in your blood before starting treatment and as needed during treatment with COBENFY. Tell your healthcare provider if you get any signs or symptoms of biliary disorders during treatment with COBENFY, including:

- stomach upset or burning (dyspepsia)
- nausea

- vomiting
- pain in the upper right part of your stomach

- Slow emptying of your stomach (decreased gastrointestinal motility). See “Do not take COBENFY if you:” You are at increased risk for getting decreased gastrointestinal motility if you have ulcerative colitis, already have problems with slow stomach emptying, and have myasthenia gravis. Tell your healthcare provider if you get any signs and symptoms of decreased gastrointestinal motility during treatment with COBENFY, including:

- constipation
- vomiting
- nausea
- stomach (abdominal) bloating

- stomach (abdominal) pain
- a feeling of fullness after eating just a few bites
- acid reflux

- Serious allergic reactions (angioedema). Angioedema may happen during treatment with COBENFY and can be life threatening. Stop taking COBENFY and call your healthcare provider or get emergency help right away if you get any of the following signs or symptoms of a serious allergic reaction during treatment with COBENFY, including:

- hives
- swelling of your face, lips, mouth, or tongue
- swelling of your throat

- hoarseness or difficulty speaking
- breathing problems

- An eye problem called narrow-angle glaucoma. See “Do not take COBENFY if you:” If you already have narrow angles in your eyes, COBENFY may cause a sudden attack (acute angle closure) of glaucoma. Tell your healthcare provider if you get any signs or symptoms of narrow-angle glaucoma during treatment with COBENFY, including:

- red eyes
- blurred vision
- seeing halos or bright colors around lights

- eye pain or discomfort
- nausea or vomiting
- severe headache

- Increases in heart rate. COBENFY may increase your heart (pulse) rate. Your healthcare provider should check your heart rate before you start treatment and during treatment as needed. Tell your healthcare provider if you get a racing or pounding feeling in your chest during treatment with COBENFY.
- Side effects in people with kidney problems. People with kidney problems may have an increased risk of getting dry mouth, constipation, stomach upset or burning, urinary tract infection, and urinary retention during treatment with COBENFY.
- Central nervous system problems. See “What should I avoid while taking COBENFY?”

The most common side effects of COBENFY include:

- nausea
- stomach upset or burning (dyspepsia)
- constipation
- vomiting
- high blood pressure

- stomach (abdominal) pain
- diarrhea
- increased heart rate
- dizziness
- heartburn (gastrointestinal reflux disease)

Your healthcare provider may lower your dose or stop treatment with COBENFY if you get certain side effects.
These are not all of the possible side effects of COBENFY.
Call your doctor for medical advice about side effects. You may report side effects to FDA at 1-800-FDA-1088.

How should I store COBENFY?

- Store COBENFY at room temperature between 68°F to 77°F (20°C to 25°C).

Keep COBENFY and all medicines out of the reach of children.

General information about the safe and effective use of COBENFY.

Medicines are sometimes prescribed for purposes other than those listed in a Patient Information leaflet. Do not use COBENFY for a condition for which it was not prescribed. Do not give your COBENFY to other people, even if they have the same symptoms that you have. It may harm them. You can ask your pharmacist or healthcare provider for information about COBENFY that is written for health professionals.

What are the ingredients in COBENFY?
Active ingredients: xanomeline and trospium chloride
Inactive ingredients: ascorbic acid, lactose monohydrate, microcrystalline cellulose, and talc

The capsule shell contains black iron oxide (only 100 mg/20 mg), hypromellose, red iron oxide, titanium dioxide, and yellow iron oxide (only 50 mg/20 mg and 100 mg/20 mg).

Marketed by:

Bristol-Myers Squibb Company

Princeton, NJ 08543 USA

COBENFY is a trademark of Karuna Therapeutics, Inc., a Bristol Myers Squibb company.

For more information, go to www.COBENFY.com or call 1-800-721-5072.

This Patient Information has been approved by the U.S. Food and Drug Administration.

Issued: 9/2024

PRINCIPAL DISPLAY PANEL - 50 mg/20 mg Capsule Bottle Label

NDC 0003-0050-60
Rx Only

COBENFY™
(xanomeline and trospium chloride) capsules

Recommended
Dosage: Take one
capsule twice daily.
See Prescribing
Information

50 mg/20 mg
60 Capsules

PRINCIPAL DISPLAY PANEL - 100 mg/20 mg Capsule Bottle Label

NDC 0003-1100-60

COBENFY™
(xanomeline and trospium chloride) capsules

100 mg/20 mg

Rx Only 60 CAPSULES

Recommended Dosage: Take one capsule
twice daily. See Prescribing Information

PRINCIPAL DISPLAY PANEL - 125 mg/30 mg Capsule Bottle Label

NDC 0003-0125-60
Rx Only

COBENFY™
(xanomeline and trospium chloride) capsules

125 mg/30 mg

Rx Only 60 Capsules

Recommended Dosage: Take on capsule
twice daily. See Prescribing Information

PRINCIPAL DISPLAY PANEL - Kit Carton

NDC 0003-5200-56

Rx Only

COBENFY™
(xanomeline and trospium chloride) capsules

50 mg/20 mg
per capsule
100 mg/20 mg
per capsule

Starter Pack

FOR ORAL USE

This Starter Pack contains 56 capsules for dosing over 28 days.
The contents of this pack are as follows:
Four - 50 mg/20 mg capsules
Fifty-two - 100 mg/20 mg capsules

PRINCIPAL DISPLAY PANEL - Sample Titration Wallet

PROFESSIONAL SAMPLE
NOT FOR RESALE
NDC 0003-5150-14

Rx Only

COBENFY™
(xanomeline and trospium chloride) capsules

50 mg/20 mg
per capsule
100 mg/20 mg
per capsule

TITRATION PACK
Days 1-2: Take one capsule
(50 mg/20 mg) twice daily
Days 3-7: Take one capsule
(100 mg/20 mg) twice daily

Contains 14 capsules:
Four - 50 mg/20 mg capsules
Ten - 100 mg/20 mg capsules